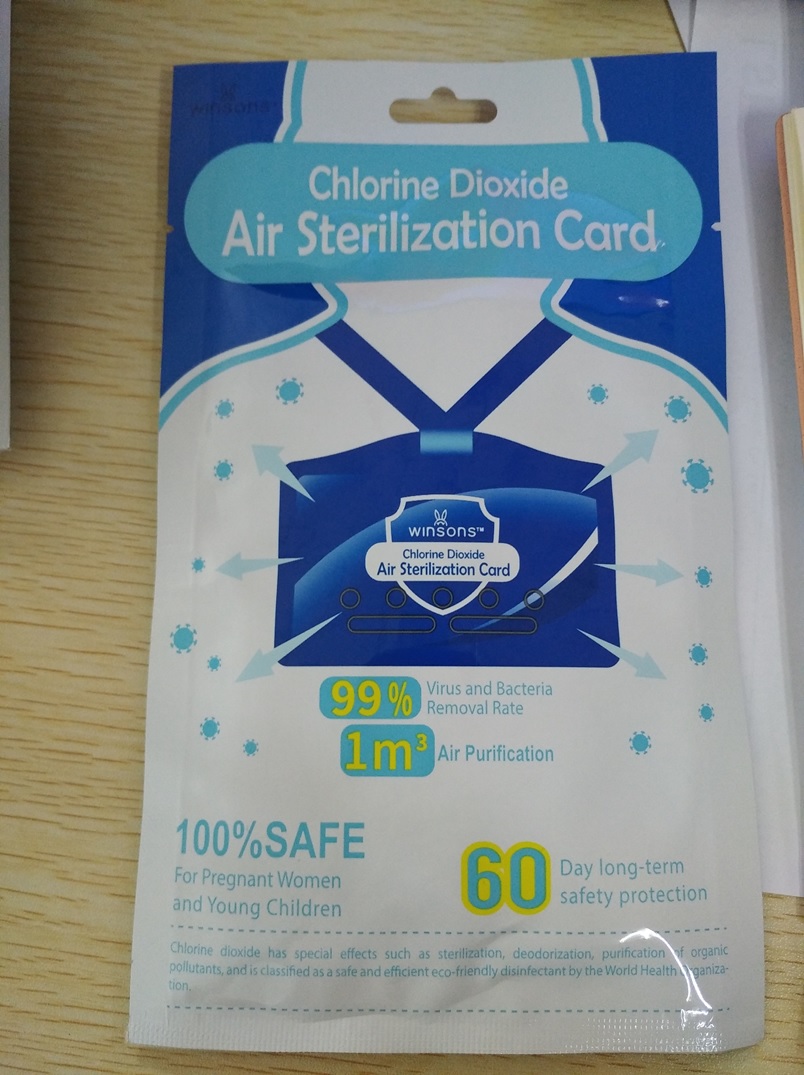 DRUG LABEL: Chlorine Dioxide Air Sterilization Card
NDC: 80694-101 | Form: POWDER
Manufacturer: Heyuan City Wingart Enterprises Co., Ltd.
Category: otc | Type: HUMAN OTC DRUG LABEL
Date: 20201001

ACTIVE INGREDIENTS: SILICON DIOXIDE 30 g/100 g
INACTIVE INGREDIENTS: POTASSIUM ALUMINUM DISILICATE; TITANIUM DIOXIDE; ALUMINUM OXIDE

Chlorine Dioxide Air Sterilization Card

Chlorine Dioxide Air Sterilization Card

Active Ingredient(s)

Silicon dioxide 30g/100g. Purpose: Antiseptic

Purpose

Antiseptic, Chlorine Dioxide Air Sterilization Card

Use

Chlorine Dioxide Air Sterilization Card to help reduce bacteria that potentially can cause disease. For use when soap and water are not available.

Warnings

For external use only. Flammable. Keep away from heat or flame

Do not use

- in children less than 2 months of age
- on open skin wounds

When using this product keep out of eyes, ears, and mouth. In case of contact with eyes, rinse eyes thoroughly with water.
Stop use and ask a doctor if irritation or rash occurs. These may be signs of a serious condition.
Keep out of reach of children. If swallowed, get medical help or contact a Poison Control Center right away.

Stop use and ask a doctor if irritation or rash occurs. These may be signs of a serious condition.

Keep out of reach of children. If swallowed, get medical help or contact a Poison Control Center right away.

Directions

- Take it with you, the gas it releases can kill bacteria
- Supervise children under 6 years of age when using this product to avoid swallowing.

Other information

- Store between 15-30C (59-86F)
- Avoid freezing and excessive heat above 40C (104F)

Inactive ingredients

Aluminium oxide
Aluminum potassium silicate
Titanium dioxide